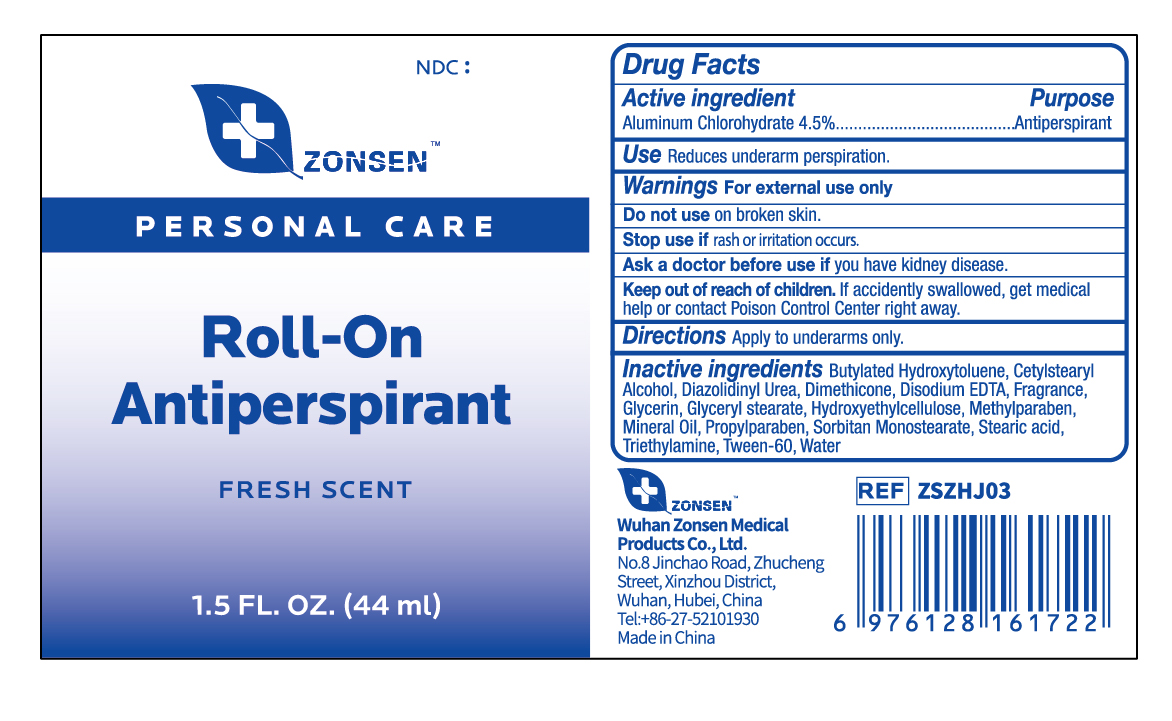 DRUG LABEL: ZONSEN Roll-On Antiperspirant
NDC: 72932-012 | Form: LOTION
Manufacturer: Wuhan Zonsen Medical Products Co., Ltd.
Category: otc | Type: HUMAN OTC DRUG LABEL
Date: 20240826

ACTIVE INGREDIENTS: ALUMINUM CHLOROHYDRATE 45 mg/1 mL
INACTIVE INGREDIENTS: MINERAL OIL; DIMETHICONE; BUTYLATED HYDROXYTOLUENE; EDETATE DISODIUM; WATER; STEARIC ACID; PROPYLPARABEN; GLYCERIN; TRIETHYLAMINE; POLYSORBATE 60; SORBITAN MONOSTEARATE; CETOSTEARYL ALCOHOL; GLYCERYL MONOSTEARATE; DIAZOLIDINYL UREA; METHYLPARABEN; HYDROXYETHYL CELLULOSE, UNSPECIFIED

Warnings

For external use only

ACTIVE INGREDIENT

Aluminum Chlorohydrate 4.5%

PURPOSE

Antiperspirant

USE

Reduces underarm perspiration.

DO NOT USE

on broken skin.

Stop use

if rash or irritation occurs.

Ask Doctor Before Use

if you have kidney disease.

Directions

Apply to underarms only

Keep Out of Reach of Children

If accidently swallowed, get medical help or contact Poison Control Center right away

Inactive Ingredient

Water, Stearic acid, Mineral Oil, Sorbitan Monostearate, Cetylstearyl Alcohol, Dimethicone, Glyceryl stearate, Butylated Hydroxytoluene, Methylparaben, Propylparaben, Glycerin, Hydroxyethyl cellulose,Disodium EDTA, Tween-60, Triethylamine, Diazolidinyl Urea, Fragrance

DOSAGE AND ADMINISTRATION

Use daily for best results.